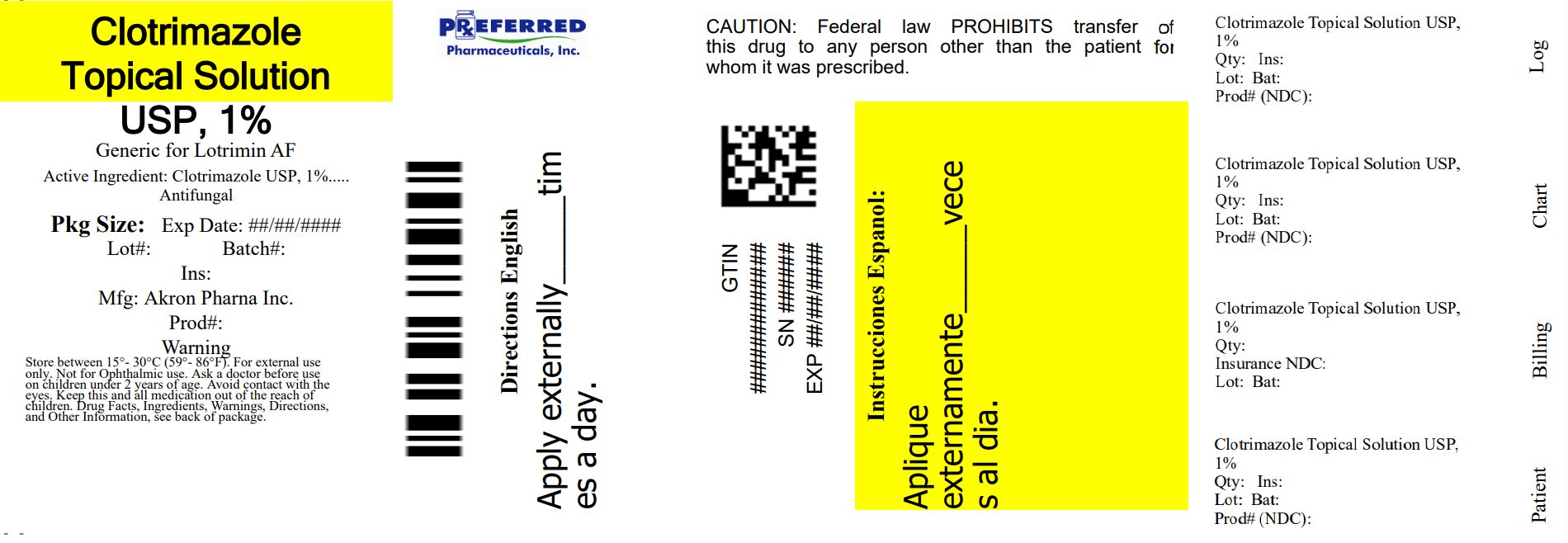 DRUG LABEL: Clotrimazole
NDC: 68788-4080 | Form: SOLUTION
Manufacturer: Preferred Pharmaceuticals Inc.
Category: otc | Type: HUMAN OTC DRUG LABEL
Date: 20260225

ACTIVE INGREDIENTS: CLOTRIMAZOLE 1 g/1 mL
INACTIVE INGREDIENTS: POLYETHYLENE GLYCOL 400

Clotrimazole Topical Solution USP,1%

Drug Facts

Active ingredient

Clotrimazole USP, 1%

Purpose

Antifungal

Uses

Cures most

- Athlete's foot (tinea pedis)
- Jock Itch (tinea cruris)
- Ringworm (tinea corporis)

Effectively relieves

- Itching
- Cracking
- Burning

Discomfort which can accompany these conditions

Warnings

For external use only

Ask a doctor before use

on children under 2 years of age

When using this product

avoid contact with eyes

Stop use and ask a doctor if

- irritation occurs
- there is no improvement within 4 weeks (for athlete's foot and ringworm) or 2 weeks (for jock itch)

Keep out of reach of children

If swallowed, get medical help or contact a Poison Control Center right away.

Directions

- This product is not effective on the scalp or nails For best results, follow directions and continue treatment for length of time indicated. For athlete's foot and ringworm: use daily for 4 weeks. For jock itch: use daily for 2 weeks.
- clean the affected area and dry thoroughly
- apply a thin layer of the product over affected area twice daily (morning and night) or as directed by a doctor
- supervise children in the use of this product

For athlete's foot: pay special attention to spaces between the toes; wear well-fitting, ventilated shoes; change shoes and socks at least once daily

Other information

- Store at 15° to 30°C (59° to 86°F)

Inactive ingredient

polyethylene glycol 400

Questions?

Please Call 1-877-225-6999

PRINCIPAL DISPLAY PANEL - 10 mL Bottle Carton

NDC 68788-4080-1

Relabeled By: Preferred Pharmaceuticals Inc.

Compare to the active ingredient of Lotrimin ®AF*

Clotrimazole Topical Solution USP,1%

Antifungal

- Relieves Itching & Burning
- Greaseless, Nonstaining

For External use only.
Not for Opthalmic use.

Keep this and all medications out of the reach of children .

Akron Pharma

10ml